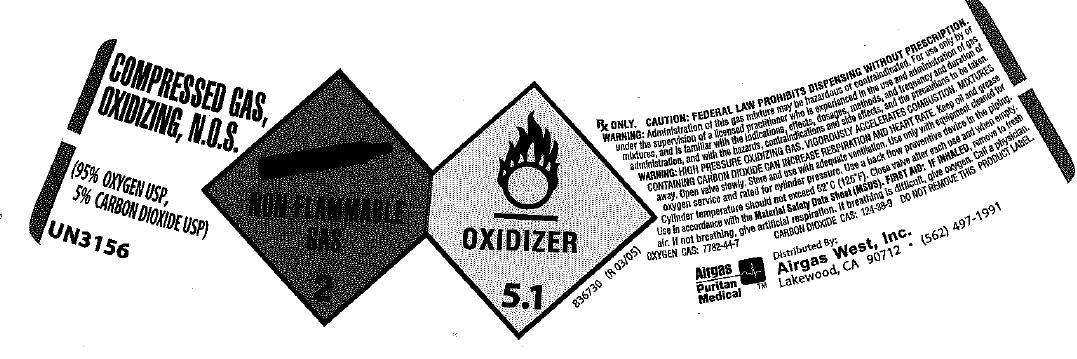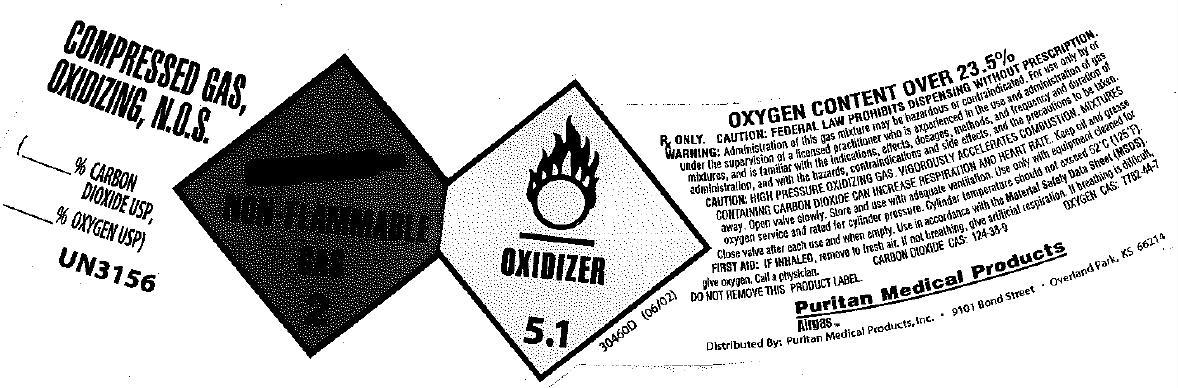 DRUG LABEL: Oxygen Carbon Dioxide Mix
NDC: 10678-008 | Form: GAS
Manufacturer: Airgas-West, Inc.
Category: prescription | Type: HUMAN PRESCRIPTION DRUG LABEL
Date: 20100430

ACTIVE INGREDIENTS: Oxygen 950 mL/1 L; Carbon Dioxide 50 mL/1 L

carbon dioxide oxygen mix

PACKAGE LABEL

COMPRESSED GAS, OXIDIZING, N.O.S.
(95% OXYGEN USP, 5% CARBON DIOXIDE USP)
UN3156
NON-FLAMMABLE 2 OXIDIZER 5.1
83670 (R 03/05)
Rx only.
CAUTION: Federal law prohibits dispensing without a prescription. WARNING: Administration of this gas mixture may be hazardous or contraindicated. For use by or under the supervision of a licensed practitioner who is experienced in the use and administration of gas mixtures and is familiar with the indications, effects, dosages, methods, and frequency and duration of administration, and with the hazards, contraindications and side effects, and the precautions to be taken.
WARNING: HIGH PRESSURE OXIDIZING LIQUID GAS. VIGOROUSLY ACCELERATES COMBUSTION. MIXTURES CONTAINING CARBON DIOXIDE CAN INCREASE RESPIRATION AND HEART RATE. Keep oil and grease away. Open valve slowly. Store and use with adequate ventilation. Use only with equipment cleaned for oxygen service and rated for cylinder pressure. Use a back flow preventive device in the piping. Cylinder temperature should not exceed 52oC(125oF). Close valve after each use and when empty. Use in accordance with the Material Safety Data Sheet (MSDS).
FIRST AID: IF INHALED, remove to fresh air. If not breathing, give artificial respiration. If breathing is difficult, give oxygen. Call a physician. OXYGEN CAS: 7782-44-7 CARBON DIOXIDE CAS: 124-38-9
DO NOT REMOVE THIS PRODUCT LABEL.
AIRGAS PURITAN MEDICAL Distributed By: Airgas West, Inc. Lakewood, CA 90712 (562) 497-1991

PACKAGE LABEL

COMPRESSED GAS, OXIDIZING, N.O.S.
(% OXYGEN USP, % CARBON DIOXIDE USP)
UN3156
NON-FLAMMABLE 2 OXIDIZER 5.1
83670 (R 03/05)
Rx only.
CAUTION: Federal law prohibits dispensing without a prescription. WARNING: Administration of this gas mixture may be hazardous or contraindicated. For use by or under the supervision of a licensed practitioner who is experienced in the use and administration of gas mixtures and is familiar with the indications, effects, dosages, methods, and frequency and duration of administration, and with the hazards, contraindications and side effects, and the precautions to be taken.
WARNING: HIGH PRESSURE OXIDIZING LIQUID GAS. VIGOROUSLY ACCELERATES COMBUSTION. MIXTURES CONTAINING CARBON DIOXIDE CAN INCREASE RESPIRATION AND HEART RATE. Keep oil and grease away. Open valve slowly. Store and use with adequate ventilation. Use only with equipment cleaned for oxygen service and rated for cylinder pressure. Use a back flow preventive device in the piping. Cylinder temperature should not exceed 52oC(125oF). Close valve after each use and when empty. Use in accordance with the Material Safety Data Sheet (MSDS).
FIRST AID: IF INHALED, remove to fresh air. If not breathing, give artificial respiration. If breathing is difficult, give oxygen. Call a physician. OXYGEN CAS: 7782-44-7 CARBON DIOXIDE CAS: 124-38-9
DO NOT REMOVE THIS PRODUCT LABEL.
AIRGAS PURITAN MEDICAL Distributed By: Airgas West, Inc. Lakewood, CA 90712 (562) 497-1991